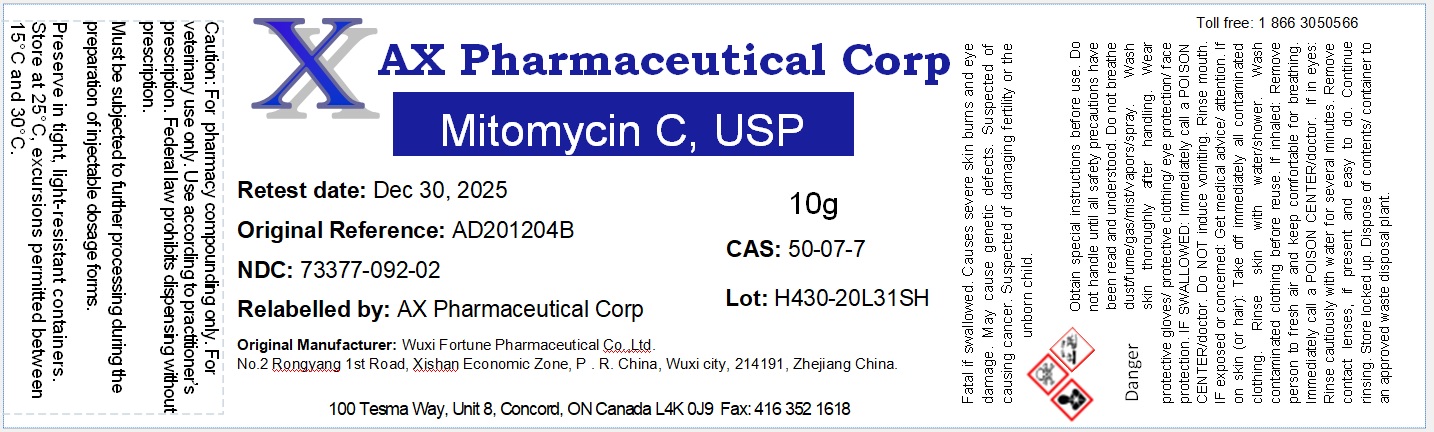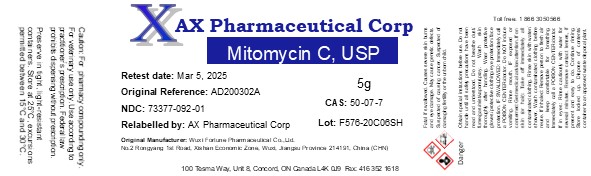 DRUG LABEL: Mitomycin C
NDC: 73377-092 | Form: POWDER
Manufacturer: AX Pharmaceutical Corp
Category: other | Type: BULK INGREDIENT - ANIMAL DRUG
Date: 20221005

ACTIVE INGREDIENTS: MITOMYCIN 1 g/1 g

Mitomycin C